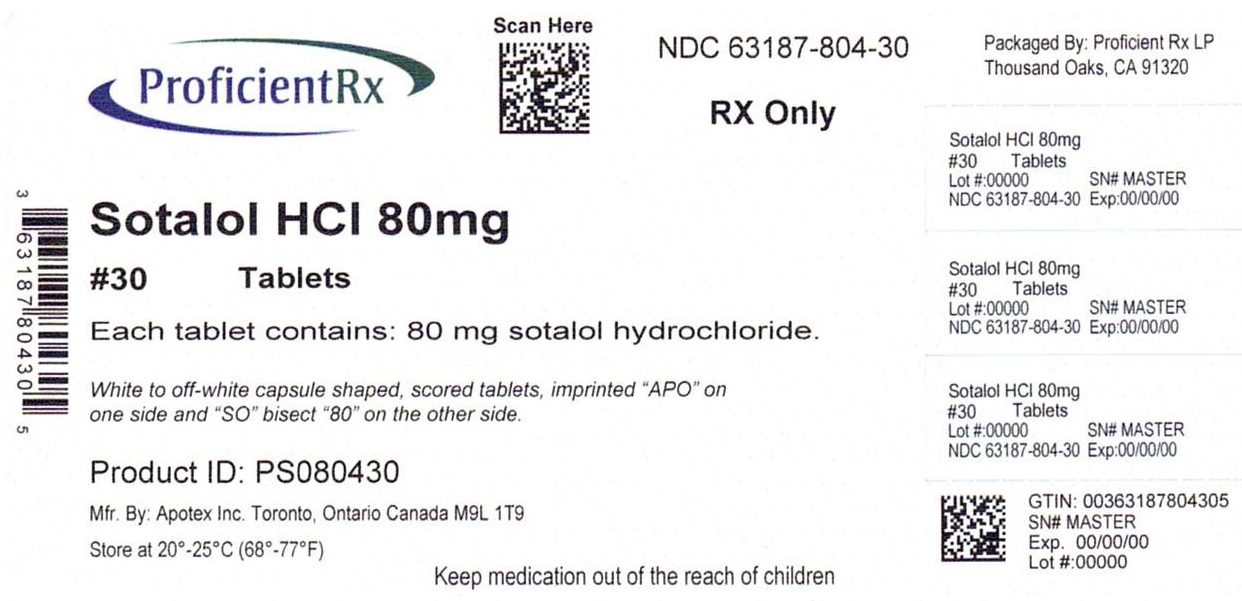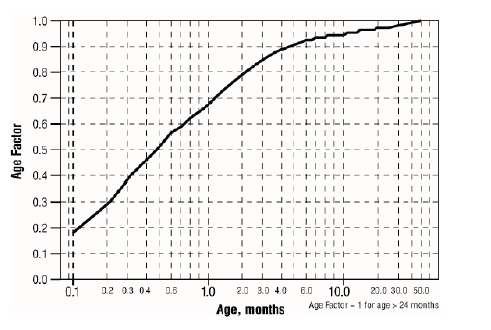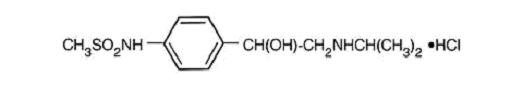 DRUG LABEL: Sotalol Hydrochloride
NDC: 63187-804 | Form: TABLET
Manufacturer: Proficient Rx LP
Category: prescription | Type: HUMAN PRESCRIPTION DRUG LABEL
Date: 20230701

ACTIVE INGREDIENTS: SOTALOL HYDROCHLORIDE 80 mg/1 1
INACTIVE INGREDIENTS: MAGNESIUM STEARATE; MICROCRYSTALLINE CELLULOSE

SOTALOL HYDROCHLORIDE TABLETS, USP
80 mg
Rx Only

BOXED WARNING

To minimize the risk of induced arrhythmia, patients initiated or reinitiated on sotalol hydrochloride tablets should be placed for a minimum of three days (on their maintenance dose) in a facility that can provide cardiac resuscitation and continuous electrocardiographic monitoring. Creatinine clearance should be calculated prior to dosing. For detailed instructions regarding dose selection and special cautions for people with renal impairment, see DOSAGE AND ADMINISTRATION. Sotalol is also indicated for the maintenance of normal sinus rhythm [delay in time to recurrence of atrial fibrillation/atrial flutter (AFIB/AFL)] in patients with symptomatic AFIB/AFL who are currently in sinus rhythm and is marketed under the brand name Betapace AF®. Sotalol hydrochloride tablets, USP are not approved for the AFIB/AFL indication and should not be substituted for Betapace AF because only Betapace AF is distributed with a patient package insert that is appropriate for patients with AFIB/AFL.

DESCRIPTION

Sotalol hydrochloride tablets, USP are an antiarrhythmic drug with Class II (beta-adrenoreceptor blocking) and Class III (cardiac action potential duration prolongation) properties. It is supplied as a white to off-white, capsule-shaped, scored tablet for oral administration. Sotalol hydrochloride is a white, crystalline solid with a molecular weight of 308.8. It is hydrophilic, soluble in water, propylene glycol and ethanol, but is only slightly soluble in chloroform. Chemically, sotalol hydrochloride is d,l-N-[4-[1-hydroxy-2-[(1-methylethyl) amino]ethyl]phenyl]methane-sulfonamide monohydrochloride. The molecular formula is C12H20N203S•HCl and is represented by the following structural formula:

Each tablet, for oral administration, contains 80 mg of sotalol hydrochloride. In addition, each tablet also contains the following inactive ingredients: magnesium stearate and microcrystalline cellulose.

CLINICAL PHARMACOLOGY

Mechanism of Action

Sotalol hydrochloride has both betaadrenoreceptor blocking (Vaughan Williams Class II) and cardiac action potential duration prolongation (Vaughan Williams Class III) antiarrhythmic properties. Sotalol hydrochloride is a racemic mixture of d- and l-sotalol. Both isomers have similar Class III antiarrhythmic effects, while the l-isomer is responsible for virtually all of the beta-blocking activity. The beta-blocking effect of sotalol is non-cardioselective, half maximal at about 80 mg/day and maximal at doses between 320 and 640 mg/day. Sotalol does not have partial agonist or membrane stabilizing activity. Although significant beta-blockade occurs at oral doses as low as 25 mg, significant Class III effects are seen only at daily doses of 160 mg and above.

In children, a Class III electrophysiologic effect can be seen at daily doses of 210 mg/m^2 body surface area (BSA). A reduction of the resting heart rate due to the beta-blocking effect of sotalol is observed at daily doses ≥ 90 mg/m^2 in children.

Electrophysiology

Sotalol hydrochloride prolongs the plateau phase of the cardiac action potential in the isolated myocyte, as well as in isolated tissue preparations of ventricular or atrial muscle (Class III activity). In intact animals it slows heart rate, decreases AV nodal conduction and increases the refractory periods of atrial and ventricular muscle and conduction tissue.

In man, the Class II (beta-blockade) electrophysiological effects of sotalol are manifested by increased sinus cycle length (slowed heart rate), decreased AV nodal conduction and increased AV nodal refractoriness. The Class III electrophysiological effects in man include prolongation of the atrial and ventricular monophasic action potentials, and effective refractory period prolongation of atrial muscle, ventricular muscle, and atrio-ventricular accessory pathways (where present) in both the anterograde and retrograde directions. With oral doses of 160 to 640 mg/day, the surface ECG shows dose-related mean increases of 40 to 100 msec in QT and 10 to 40 msec in QTc (see WARNINGS for description of relationship between QTc and Torsade de Pointes type arrhythmias). No significant alteration in QRS interval is observed.

In a small study (n=25) of patients with implanted defibrillators treated concurrently with sotalol, the average defibrillatory threshold was 6 joules (range 2 to 15 joules) compared to a mean of 16 joules for a nonrandomized comparative group primarily receiving amiodarone.

Twenty-five children in an unblinded, multicenter trial with supraventricular (SVT) and/or ventricular (VT) tachyarrhythmias, aged between 3 days and 12 years (mostly neonates and infants), received an ascending titration regimen with daily doses of 30, 90 and 210 mg/m^2 with dosing every 8 hours for a total 9 doses. During steady-state, the respective average increases above baseline of the QTc interval, in msec (%), were 2(+1%), 14(+4%) and 29(+7%) msec at the 3 dose levels. The respective mean maximum increases above baseline of the QTc interval, in msec (%), were 23(+6%), 36(+9%) and 55(+14%) msec at the 3 dose levels. The steadystate percent increases in the RR interval were 3, 9 and 12%. The smallest children (BSA<0.33m^2) showed a tendency for larger Class III effects (ΔQTc) and an increased frequency of prolongations of the QTc interval as compared with larger children (BSA≥0.33m^2). The beta-blocking effects also tended to be greater in the smaller children (BSA<0.33m^2). Both the Class III and beta-blocking effects of sotalol were linearly related with the plasma concentrations.

Hemodynamics

In a study of systemic hemodynamic function measured invasively in 12 patients with a mean LV ejection fraction of 37% and ventricular tachycardia (9 sustained and 3 non-sustained), a median dose of 160 mg twice daily of sotalol hydrochloride produced a 28% reduction in heart rate and a 24% decrease in cardiac index at 2 hours post dosing at steady-state. Concurrently, systemic vascular resistance and stroke volume showed nonsignificant increases of 25% and 8%, respectively. Pulmonary capillary wedge pressure increased significantly from 6.4 mmHg to 11.8 mmHg in the 11 patients who completed the study. One patient was discontinued because of worsening congestive heart failure. Mean arterial pressure, mean pulmonary artery pressure and stroke work index did not significantly change. Exercise and isoproterenol induced tachycardia are antagonized by sotalol, and total peripheral resistance increases by a small amount.

In hypertensive patients, sotalol hydrochloride produces significant reductions in both systolic and diastolic blood pressures. Although sotalol hydrochloride is usually well-tolerated hemodynamically, caution should be exercised in patients with marginal cardiac compensation as deterioration in cardiac performance may occur (see WARNINGS, Congestive Heart Failure).

Clinical Studies

Sotalol hydrochloride has been studied in life-threatening and less severe arrhythmias. In patients with frequent premature ventricular complexes (VPC), sotalol hydrochloride was significantly superior to placebo in reducing VPCs, paired VPCs and non-sustained ventricular tachycardia (NSVT); the response was dose-related through 640 mg/day with 80 to 85% of patients having at least a 75% reduction of VPCs. Sotalol hydrochloride was also superior, at the doses evaluated, to propranolol (40 to 80 mg TID) and similar to quinidine (200 to 400 mg QID) in reducing VPCs. In patients with lifethreatening arrhythmias [sustained ventricular tachycardia/fibrillation (VT/VF)], sotalol hydrochloride was studied acutely [by suppression of programmed electrical stimulation (PES) induced VT and by suppression of Holter monitor evidence of sustained VT] and, in acute responders, chronically.

In a double-blind, randomized comparison of sotalol and procainamide given intravenously (total of 2 mg/kg sotalol vs. 19 mg/kg of procainamide over 90 minutes), sotalol suppressed PES induction in 30% of patients vs. 20% for procainamide (p=0.2).

In a randomized clinical trial [Electrophysiologic Study Versus Electrocardiographic Monitoring (ESVEM) Trial] comparing choice of antiarrhythmic therapy by PES suppression vs. Holter monitor selection (in each case followed by treadmill exercise testing) in patients with a history of sustained VT/VF who were also inducible by PES, the effectiveness acutely and chronically of sotalol hydrochloride was compared with 6 other drugs (procainamide, quinidine, mexiletine, propafenone, imipramine and pirmenol). Overall response, limited to first randomized drug, was 39% for sotalol and 30% for the pooled other drugs. Acute response rate for first drug randomized using suppression of PES induction was 36% for sotalol vs. a mean of 13% for the other drugs. Using the Holter monitoring endpoint (complete suppression of sustained VT, 90% suppression of NSVT, 80% suppression of VPC pairs, and at least 70% suppression of VPCs), sotalol yielded 41% response vs. 45% for the other drugs combined. Among responders placed on long-term therapy identified acutely as effective (by either PES or Holter), sotalol, when compared to the pool of other drugs, had the lowest two-year mortality (13% vs. 22%), the lowest two-year VT recurrence rate (30% vs. 60%), and the lowest withdrawal rate (38% vs. about 75 to 80%). The most commonly used doses of sotalol hydrochloride in this trial were 320 to 480 mg/day (66% of patients), with 16% receiving 240 mg/day or less and 18% receiving 640 mg or more.

It cannot be determined, however, in the absence of a controlled comparison of sotalol vs. no pharmacologic treatment (e.g., in patients with implanted defibrillators) whether sotalol response causes improved survival or identifies a population with a good prognosis.

In a large double-blind, placebo controlled secondary prevention (postinfarction) trial (n=1,456), sotalol hydrochloride was given as a non-titrated initial dose of 320 mg once daily. Sotalol did not produce a significant increase in survival (7.3% mortality on sotalol vs. 8.9% on placebo, p=0.3), but overall did not suggest an adverse effect on survival. There was, however, a suggestion of an early (i.e., first 10 days) excess mortality (3% on sotalol vs. 2% on placebo). In a second small trial (n=17 randomized to sotalol) where sotalol was administered at high doses (e.g., 320 mg twice daily) to high-risk post-infarction patients (ejection fraction <40% and either >10 VPC/hr or VT on Holter), there were 4 fatalities and 3 serious hemodynamic/electrical adverse events within two weeks of initiating sotalol.

Pharmacokinetics

In healthy subjects, the oral bioavailability of sotalol hydrochloride is 90 to 100%. After oral administration, peak plasma concentrations are reached in 2.5 to 4 hours, and steady-state plasma concentrations are attained within 2 to 3 days (i.e., after 5 to 6 doses when administered twice daily). Over the dosage range 160 to 640 mg/day sotalol hydrochloride displays dose proportionality with respect to plasma concentrations. Distribution occurs to a central (plasma) and to a peripheral compartment, with a mean elimination half-life of 12 hours. Dosing every 12 hours results in trough plasma concentrations which are approximately one-half of those at peak.

Sotalol hydrochloride does not bind to plasma proteins and is not metabolized. Sotalol hydrochloride shows very little intersubject variability in plasma levels. The pharmacokinetics of the d and l enantiomers of sotalol are essentially identical. Sotalol hydrochloride crosses the blood brain barrier poorly. Excretion is predominantly via the kidney in the unchanged form, and therefore lower doses are necessary in conditions of renal impairment (see DOSAGE AND ADMINISTRATION). Age per se does not significantly alter the pharmacokinetics of sotalol hydrochloride, but impaired renal function in geriatric patients can increase the terminal elimination half-life, resulting in increased drug accumulation. The absorption of sotalol hydrochloride was reduced by approximately 20% compared to fasting when it was administered with a standard meal. Since sotalol hydrochloride is not subject to first-pass metabolism, patients with hepatic impairment show no alteration in clearance of sotalol.

The combined analysis of two unblinded, multicenter trials (a single dose and a multiple dose study) with 59 children, aged between 3 days and 12 years, showed the pharmacokinetics of sotalol to be first order. A daily dose of 30 mg/m^2 of sotalol was administered in the single dose study and daily doses of 30, 90 and 210 mg/m^2 were administered q 8h in the multi-dose study. After rapid absorption with peak levels occurring on average between 2 to 3 hours following administration, sotalol was eliminated with a mean half life of 9.5 hours. Steady-state was reached after 1 to 2 days. The average peak to trough concentration ratio was 2. BSA was the most important covariate and more relevant than age for the pharmacokinetics of sotalol.The smallest children (BSA<0.33m^2) exhibited a greater drug exposure (+59%) than the larger children who showed a uniform drug concentration profile. The intersubject variation for oral clearance was 22%.

INDICATIONS AND USAGE

Sotalol hydrochloride tablets, USP are indicated for the treatment of documented ventricular arrhythmias, such as sustained ventricular tachycardia, that in the judgment of the physician are life-threatening. Because of the proarrhythmic effects of sotalol hydrochloride tablets, USP (see WARNINGS), including a 1.5 to 2% rate of Torsade de Pointes or new VT/VF in patients with either NSVT or supraventricular arrhythmias, its use in patients with less severe arrhythmias, even if the patients are symptomatic, is generally not recommended. Treatment of patients with asymptomatic ventricular premature contractions should be avoided.

Initiation of sotalol hydrochloride treatment or increasing doses, as with other antiarrhythmic agents used to treat life-threatening arrhythmias, should be carried out in the hospital. The response to treatment should then be evaluated by a suitable method (e.g., PES or Holter monitoring) prior to continuing the patient on chronic therapy. Various approaches have been used to determine the response to antiarrhythmic therapy, including sotalol hydrochloride tablets, USP.

In the ESVEM Trial, response by Holter monitoring was tentatively defined as 100% suppression of ventricular tachycardia, 90% suppression of nonsustained VT, 80% suppression of paired VPCs, and 75% suppression of total VPCs in patients who had at least 10 VPCs/hour at baseline; this tentative response was confirmed if VT lasting 5 or more beats was not observed during treadmill exercise testing using a standard Bruce protocol. The PES protocol utilized a maximum of three extrastimuli at three pacing cycle lengths and two right ventricular pacing sites. Response by PES was defined as prevention of induction of the following: 1) monomorphic VT lasting over 15 seconds; 2) non-sustained polymorphic VT containing more than 15 beats of monomorphic VT in patients with a history of monomorphic VT; 3) polymorphic VT or VF greater than 15 beats in patients with VF or a history of aborted sudden death without monomorphic VT; and 4) two episodes of polymorphic VT or VF of greater than 15 beats in a patient presenting with monomorphic VT. Sustained VT or NSVT producing hypotension during the final treadmill test was considered a drug failure.

In a multicenter open-label long-term study of sotalol in patients with life-threatening ventricular arrhythmias which had proven refractory to other antiarrhythmic medications, response by Holter monitoring was defined as in ESVEM. Response by PES was defined as non-inducibility of sustained VT by at least double extrastimuli delivered at a pacing cycle length of 400 msec. Overall survival and arrhythmia recurrence rates in this study were similar to those seen in ESVEM, although there was no comparative group to allow a definitive assessment of outcome.

Antiarrhythmic drugs have not been shown to enhance survival in patients with ventricular arrhythmias.

Sotalol is also indicated for the maintenance of normal sinus rhythm [delay in time to recurrence of atrial fibrillation/atrial flutter (AFIB/AFL)] in patients with symptomatic AFIB/AFL who are currently in sinus rhythm and is marketed under the brand name Betapace AF (sotalol hydrochloride, tablets, USP). Sotalol hydrochloride tablets, USP is not approved for the AFIB/AFL indication and should not be substituted for Betapace AF because only Betapace AF is distributed with a patient package insert that is appropriate for patients with AFIB/AFL.

CONTRAINDICATIONS

Sotalol hydrochloride is contraindicated in patients with bronchial asthma, sinus bradycardia, second and third degree AV block, unless a functioning pacemaker is present, congenital or acquired long QT syndromes, cardiogenic shock, uncontrolled congestive heart failure, and previous evidence of hypersensitivity to sotalol.

WARNINGS

Mortality

The National Heart, Lung, and Blood Institute's Cardiac Arrhythmia Suppression Trial I (CAST I) was a long-term, multi-center, double-blind study in patients with asymptomatic, non-life-threatening ventricular arrhythmias, 1 to 103 weeks after acute myocardial infarction. Patients in CAST I were randomized to receive placebo or individually optimized doses of encainide, flecainide, or moricizine. The Cardiac Arrhythmia Suppression Trial II (CAST II) was similar, except that the recruited patients had had their index infarction 4 to 90 days before randomization, patients with left ventricular ejection fractions greater than 40% were not admitted, and the randomized regimens were limited to placebo and moricizine.

CAST I was discontinued after an average time-on-treatment of 10 months, and CAST II was discontinued after an average time-on-treatment of 18 months. As compared to placebo treatment, all three active therapies were associated with increases in short-term (14-day) mortality, and encainide and flecainide were associated with significant increases in longer-term mortality as well. The longer-term mortality rate associated with moricizine treatment could not be statistically distinguished from that associated with placebo.

The applicability of these results to other populations (e.g., those without recent myocardial infarction) and to other than Class I antiarrhythmic agents is uncertain. Sotalol hydrochloride is devoid of Class I effects, and in a large (n=1,456) controlled trial in patients with a recent myocardial infarction, who did not necessarily have ventricular arrhythmias, sotalol did not produce increased mortality at doses up to 320 mg/day (see Clinical Studies). On the other hand, in the large postinfarction study using a non-titrated initial dose of 320 mg once daily and in a second small randomized trial in high-risk post-infarction patients treated with high doses (320 mg BID), there have been suggestions of an excess of early sudden deaths.

Proarrhythmia

Like other antiarrhythmic agents, sotalol can provoke new or worsened ventricular arrhythmias in some patients, including sustained ventricular tachycardia or ventricular fibrillation, with potentially fatal consequences. Because of its effect on cardiac repolarization (QTc interval prolongation), Torsade de Pointes, a polymorphic ventricular tachycardia with prolongation of the QT interval and a shifting electrical axis is the most common form of proarrhythmia associated with sotalol, occurring in about 4% of high risk (history of sustained VT/VF) patients. The risk of Torsade de Pointes progressively increases with prolongation of the QT interval, and is worsened also by reduction in heart rate and reduction in serum potassium (see Electrolyte Disturbances).

Because of the variable temporal recurrence of arrhythmias, it is not always possible to distinguish between a new or aggravated arrhythmic event and the patient’s underlying rhythm disorder. (Note, however, that Torsade de Pointes is usually a drug-induced arrhythmia in people with an initially normal QTc.) Thus, the incidence of drug-related events cannot be precisely determined, so that the occurrence rates provided must be considered approximations. Note also that drug-induced arrhythmias may often not be identified, particularly if they occur long after starting the drug, due to less frequent monitoring. It is clear from the NIH-sponsored CAST (see WARNINGS, Mortality) that some antiarrhythmic drugs can cause increased sudden death mortality, presumably due to new arrhythmias or asystole, that do not appear early in treatment but that represent a sustained increased risk.

Overall in clinical trials with sotalol, 4.3% of 3257 patients experienced a new or worsened ventricular arrhythmia. Of this 4.3%, there was new or worsened sustained ventricular tachycardia in approximately 1% of patients and Torsade de Pointes in 2.4%. Additionally, in approximately 1% of patients, deaths were considered possibly drug-related; such cases, although difficult to evaluate, may have been associated with proarrhythmic events. In patients with a history of sustained ventricular tachycardia, the incidence of Torsade de Pointes was 4% and worsened VT in about 1%; in patients with other, less serious, ventricular arrhythmias and supraventricular arrhythmias, the incidence of Torsade de Pointes was 1% and 1.4%, respectively.

Torsade de Pointes arrhythmias were dose related, as is the prolongation of QT (QTc) interval, as shown in the table below.

Percent Incidence of Torsade de Pointes and Mean QTc Interval by Dose For Patients With Sustained VT/VF
Daily Dose (mg) | Incidence of Torsade de Pointes | Mean QTca (msec)
80 | 0 (69)b | 463 (17)
160 | 0.5 (832) | 467 (181)
320 | 1.6 (835) | 473 (344)
480 | 4.4 (459) | 483 (234)
640 | 3.7 (324) | 490 (185)
>640 | 5.8 (103) | 512 (62)

a) highest on-therapy value

In addition to dose and presence of sustained VT, other risk factors for Torsade de Pointes were gender (females had a higher incidence), excessive prolongation of the QTc interval (see table below) and history of cardiomegaly or congestive heart failure. Patients with sustained ventricular tachycardia and a history of congestive heart failure appear to have the highest risk for serious proarrhythmia (7%). Of the patients experiencing Torsade de Pointes, approximately two-thirds spontaneously reverted to their baseline rhythm. The others were either converted electrically (D/C cardioversion or overdrive pacing) or treated with other drugs (see OVERDOSAGE). It is not possible to determine whether some sudden deaths represented episodes of Torsade de Pointes, but in some instances sudden death did follow a documented episode of Torsade de Pointes. Although sotalol therapy was discontinued in most patients experiencing Torsade de Pointes, 17% were continued on a lower dose.

Nonetheless, sotalol should be used with particular caution if the QTc is greater than 500 msec on-therapy and serious consideration should be given to reducing the dose or discontinuing therapy when the QTc exceeds 550 msec. Due to the multiple risk factors associated with Torsade de Pointes, however, caution should be exercised regardless of the QTc interval. The table below relates the incidence of Torsade de Pointes to on-therapy QTc and change in QTc from baseline. It should be noted, however, that the highest on-therapy QTc was in many cases the one obtained at the time of the Torsade de Pointes event, so that the table overstates the predictive value of a high QTc.

Relationship Between QTc Interval Prolongation and Torsade de Pointes
On-Therapy QTc Interval (msec) | Incidence of Torsade de Pointes | Change in QTc Interval From Baseline (msec) | Incidence of Torsade de Pointes
< 500 | 1.3% (1787) | < 65 | 1.6% (1516)
500-525 | 3.4% (236) | 65-80 | 3.2% (158)
525-550 | 5.6% (125) | 80-100 | 4.1% (146)
>550 | 10.8% (157) | 100-130 | 5.2% (115)
 |  | > 130 | 7.1% (99)
() Number of patients assessed

Proarrhythmic events must be anticipated not only on initiating therapy, but with every upward dose adjustment. Proarrhythmic events most often occur within 7 days of initiating therapy or of an increase in dose; 75% of serious proarrhythmias (Torsade de Pointes and worsened VT) occurred within 7 days of initiating sotalol therapy, while 60% of such events occurred within 3 days of initiation or a dosage change. Initiating therapy at 80 mg BID with gradual upward dose titration and appropriate evaluations for efficacy (e.g., PES or Holter) and safety (e.g., QT interval, heart rate and electrolytes) prior to dose escalation, should reduce the risk of proarrhythmia. Avoiding excessive accumulation of sotalol in patients with diminished renal function, by appropriate dose reduction, should also reduce the risk of proarrhythmia (see DOSAGE AND ADMINISTRATION).

Congestive Heart Failure

Sympathetic stimulation is necessary in supporting circulatory function in congestive heart failure, and beta-blockade carries the potential hazard of further depressing myocardial contractility and precipitating more severe failure. In patients who have congestive heart failure controlled by digitalis and/or diuretics, sotalol hydrochloride tablets should be administered cautiously. Both digitalis and sotalol slow AV conduction. As with all beta-blockers, caution is advised when initiating therapy in patients with any evidence of left ventricular dysfunction. In premarketing studies, new or worsened congestive heart failure (CHF) occurred in 3.3% (n=3257) of patients and led to discontinuation in approximately 1% of patients receiving sotalol. The incidence was higher in patients presenting with sustained ventricular tachycardia/fibrillation (4.6%, n=1363), or a prior history of heart failure (7.3%, n=696). Based on a lifetable analysis, the one-year incidence of new or worsened CHF was 3% in patients without a prior history and 10% in patients with a prior history of CHF. NYHA Classification was also closely associated to the incidence of new or worsened heart failure while receiving sotalol (1.8% in 1395 Class I patients, 4.9% in 1254 Class II patients and 6.1% in 278 Class III or IV patients).

Electrolyte Disturbances

Sotalol should not be used in patients with hypokalemia or hypomagnesemia prior to correction of imbalance, as these conditions can exaggerate the degree of QT prolongation, and increase the potential for Torsade de Pointes. Special attention should be given to electrolyte and acid-base balance in patients experiencing severe or prolonged diarrhea or patients receiving concomitant diuretic drugs.

Conduction Disturbances

Excessive prolongation of the QT interval (>550 msec) can promote serious arrhythmias and should be avoided (see Proarrhythmia above). Sinus bradycardia (heart rate less than 50 bpm) occurred in 13% of patients receiving sotalol in clinical trials, and led to discontinuation in about 3% of patients. Bradycardia itself increases the risk of Torsade de Pointes. Sinus pause, sinus arrest and sinus node dysfunction occur in less than 1% of patients. The incidence of 2nd- or 3rd-degree AV block is approximately 1%.

Recent Acute MI

Sotalol can be used safely and effectively in the long-term treatment of life-threatening ventricular arrhythmias following a myocardial infarction. However, experience in the use of sotalol to treat cardiac arrhythmias in the early phase of recovery from acute MI is limited and at least at high initial doses is not reassuring (see WARNINGS, Mortality). In the first 2 weeks post-MI caution is advised and careful dose titration is especially important, particularly in patients with markedly impaired ventricular function.

The following warnings are related to the beta-blocking activity of sotalol.

Abrupt Withdrawal

Hypersensitivity to catecholamines has been observed in patients withdrawn from beta-blocker therapy. Occasional cases of exacerbation of angina pectoris, arrhythmias and, in some cases, myocardial infarction have been reported after abrupt discontinuation of beta-blocker therapy. Therefore, it is prudent when discontinuing chronically administered sotalol hydrochloride tablets, particularly in patients with ischemic heart disease, to carefully monitor the patient and consider the temporary use of an alternate beta-blocker if appropriate. If possible, the dosage of sotalol hydrochloride tablets should be gradually reduced over a period of one to two weeks. If angina or acute coronary insufficiency develops, appropriate therapy should be instituted promptly. Patients should be warned against interruption or discontinuation of therapy without the physician’s advice. Because coronary artery disease is common and may be unrecognized in patients receiving sotalol hydrochloride tablets, abrupt discontinuation in patients with arrhythmias may unmask latent coronary insufficiency.

Non-Allergic Bronchospasm (e.g., chronic bronchitis and emphysema)

PATIENTS WITH BRONCHOSPASTIC DISEASES SHOULD IN GENERAL NOT RECEIVE BETA-BLOCKERS. It is prudent, if sotalol hydrochloride tablets are to be administered, to use the smallest effective dose, so that inhibition of bronchodilation produced by endogenous or exogenous catecholamine stimulation of beta 2 receptors may be minimized.

Anaphylaxis

While taking beta-blockers, patients with a history of anaphylactic reaction to a variety of allergens may have a more severe reaction on repeated challenge, either accidental, diagnostic or therapeutic. Such patients may be unresponsive to the usual doses of epinephrine used to treat the allergic reaction.

Major Surgery

Chronically administered beta-blocking therapy should not be routinely withdrawn prior to major surgery, however the impaired ability of the heart to respond to reflex adrenergic stimuli may augment the risks of general anesthesia and surgical procedures.

Diabetes

In patients with diabetes (especially labile diabetes) or with a history of episodes of spontaneous hypoglycemia, sotalol hydrochloride tablets should be given with caution since beta-blockade may mask some important premonitory signs of acute hypoglycemia; e.g., tachycardia.

Sick Sinus Syndrome

Sotalol hydrochloride tablets should be used only with extreme caution in patients with sick sinus syndrome associated with symptomatic arrhythmias, because it may cause sinus bradycardia, sinus pauses or sinus arrest.

Thyrotoxicosis

Beta-blockade may mask certain clinical signs (e.g., tachycardia) of hyperthyroidism. Patients suspected of developing thyrotoxicosis should be managed carefully to avoid abrupt withdrawal of beta-blockade which might be followed by an exacerbation of symptoms of hyperthyroidism, including thyroid storm.

PRECAUTIONS

Renal Impairment

Sotalol hydrochloride is mainly eliminated via the kidneys through glomerular filtration and to a small degree by tubular secretion. There is a direct relationship between renal function, as measured by serum creatinine or creatinine clearance, and the elimination rate of sotalol. Guidance for dosing in conditions of renal impairment can be found under DOSAGE AND ADMINISTRATION.

Drug Interactions

Drugs undergoing CYP450 metabolism

Sotalol is primarily eliminated by renal excretion; therefore, drugs that are metabolized by CYP450 are not expected to alter the pharmacokinetics of sotalol. Sotalol is not expected to inhibit or induce any CYP450 enzymes; therefore, it is not expected to alter the PK of drugs that are metabolized by these enzymes.

Antiarrhythmics

Class Ia antiarrhythmic drugs, such as disopyramide, quinidine and procainamide and other Class III drugs (e.g., amiodarone) are not recommended as concomitant therapy with sotalol, because of their potential to prolong refractoriness (see WARNINGS). There is only limited experience with the concomitant use of Class Ib or Ic antiarrhythmics. Additive Class II effects would also be anticipated with the use of other beta-blocking agents concomitantly with sotalol.

Digoxin

Single and multiple doses of sotalol do not substantially affect serum digoxin levels. Proarrhythmic events were more common in sotalol treated patients also receiving digoxin; it is not clear whether this represents an interaction or is related to the presence of CHF, a known risk factor for proarrhythmia, in the patients receiving digoxin. Both digitalis glycosides and beta-blockers slow atrioventricular conduction and decrease heart rate. Concomitant use can increase the risk of bradycardia.

Calcium-blocking drugs

Sotalol should be administered with caution in conjunction with calcium-blocking drugs because of possible additive effects on atrioventricular conduction or ventricular function. Additionally, concomitant use of these drugs may have additive effects on blood pressure, possibly leading to hypotension.

Catecholamine-depleting agents

Concomitant use of catecholamine‑-depleting drugs, such as reserpine and guanethidine, with a beta-blocker may produce an excessive reduction of resting sympathetic nervous tone. Patients treated with sotalol plus a catecholamine depletor should therefore be closely monitored for evidence of hypotension and/or marked bradycardia which may produce syncope.

Insulin and oral antidiabetics

Hyperglycemia may occur, and the dosage of insulin or antidiabetic drugs may require adjustment. Symptoms of hypoglycemia may be masked.

Beta-2-receptor stimulants

Beta-agonists such as salbutamol, terbutaline and isoprenaline may have to be administered in increased dosages when used concomitantly with sotalol.

Clonidine

Beta-blocking drugs may potentiate the rebound hypertension sometimes observed after discontinuation of clonidine; therefore, caution is advised when discontinuing clonidine in patients receiving sotalol.

Other

No pharmacokinetic interactions were observed with hydrochlorothiazide or warfarin.

Antacids

Administration of sotalol within 2 hours of antacids containing aluminum oxide and magnesium hydroxide should be avoided because it may result in a reduction in Cmax and AUC of 26% and 20%, respectively and consequently in a 25% reduction in the bradycardic effect at rest. Administration of the antacid two hours after sotalol has no effect on the pharmacokinetics or pharmacodynamics of sotalol.

Drugs prolonging the QT interval

Sotalol should be administered with caution in conjunction with other drugs known to prolong the QT interval such as Class I and Class III antiarrhythmic agents, phenothiazines, tricyclic antidepressants, astemizole, bepridil, certain oral macrolides, and certain quinolone antibiotics (see WARNINGS).

Drug/Laboratory Test Interactions

The presence of sotalol in the urine may result in falsely elevated levels of urinary metanephrine when measured by fluorimetric or photometric methods. In screening patients suspected of having a pheochromocytoma and being treated with sotalol, a specific method, such as a high performance liquid chromatographic assay with solid phase extraction (e.g., J. Chromatogr. 385:241, 1987) should be employed in determining levels of catecholamines.

Carcinogenesis, Mutagenesis, Impairment of Fertility

No evidence of carcinogenic potential was observed in rats during a 24-month study at 137 to 275 mg/kg/day (approximately 30 times the maximum recommended human oral dose (MRHD) as mg/kg or 5 times the MRHD as mg/m^2) or in mice, during a 24-month study at 4141 to 7122 mg/kg/day (approximately 450 to 750 times the MRHD as mg/kg or 36 to 63 times the MRHD as mg/m^2).

Sotalol has not been evaluated in any specific assay of mutagenicity or clastogenicity.

No significant reduction in fertility occurred in rats at oral doses of 1000 mg/kg/day (approximately 100 times the MRHD as mg/kg or 9 times the MRHD as mg/m^2) prior to mating, except for a small reduction in the number of offspring per litter.

Pregnancy Category B

Reproduction studies in rats and rabbits during organogenesis at 100 and 22 times the MRHD as mg/kg (9 and 7 times the MRHD as mg/m^2), respectively, did not reveal any teratogenic potential associated with sotalol hydrochloride. In rabbits, a high dose of sotalol hydrochloride (160 mg/kg/day) at 16 times the MRHD as mg/kg (6 times the MRHD as mg/m^2) produced a slight increase in fetal death likely due to maternal toxicity. Eight times the maximum dose (80 mg/kg/day or 3 times the MRHD as mg/m^2) did not result in an increased incidence of fetal deaths. In rats, 1000 mg/kg/day sotalol hydrochloride, 100 times the MRHD (18 times the MRHD as mg/m^2), increased the number of early resorptions, while at 14 times the maximum dose (2.5 times the MRHD as mg/m^2), no increase in early resorptions was noted. However, animal reproduction studies are not always predictive of human response.

Although there are no adequate and well-controlled studies in pregnant women, sotalol hydrochloride has been shown to cross the placenta, and is found in amniotic fluid. There has been a report of subnormal birth weight with sotalol. Therefore, sotalol hydrochloride tablets should be used during pregnancy only if the potential benefit outweighs the potential risk.

Nursing Mothers

Sotalol is excreted in the milk of laboratory animals and has been reported to be present in human milk. Because of the potential for adverse reactions in nursing infants from sotalol, a decision should be made whether to discontinue nursing or to discontinue the drug, taking into account the importance of the drug to the mother.

Pediatric Use

The safety and effectiveness of sotalol in children have not been established. However, the Class III electrophysiologic and beta-blocking effects, the pharmacokinetics, and the relationship between the effects (QTc interval and resting heart rate) and drug concentrations have been evaluated in children aged between 3 days and 12 years old (see CLINICAL PHARMACOLOGY).

ADVERSE REACTIONS

During premarketing trials, 3186 patients with cardiac arrhythmias (1363 with sustained ventricular tachycardia) received oral sotalol, of whom 2451 received the drug for at least two weeks. The most important adverse effects are Torsade de Pointes and other serious new ventricular arrhythmias (see WARNINGS), occurring at rates of almost 4% and 1%, respectively, in the VT/VF population. Overall, discontinuation because of unacceptable side-effects was necessary in 17% of all patients in clinical trials, and in 13% of patients treated for at least two weeks. The most common adverse reactions leading to discontinuation of sotalol are as follows: fatigue 4%, bradycardia (less than 50 bpm) 3%, dyspnea 3%, proarrhythmia 3%, asthenia 2%, and dizziness 2%.

Occasional reports of elevated serum liver enzymes have occurred with sotalol therapy but no cause and effect relationship has been established. One case of peripheral neuropathy which resolved on discontinuation of sotalol and recurred when the patient was rechallenged with the drug was reported in an early dose tolerance study. Elevated blood glucose levels and increased insulin requirements can occur in diabetic patients.

The following table lists as a function of dosage the most common (incidence of 2% or greater) adverse events, regardless of relationship to therapy and the percent of patients discontinued due to the event, as collected from clinical trials involving 1292 patients with sustained VT/VF.

Incidence (%) of Adverse Events and Discontinuations
DAILY DOSE
Body System | 160 mg; (n = 832) | 240 mg; (n = 263) | 320 mg; (n = 835) | 480 mg; (n = 459) | 640 mg; (n = 324) | Any Dosea; (n = 1292) | % Patients Discontinued (n = 1292)
Body as a whole
infection | 1 | 2 | 2 | 2 | 3 | 4 | < 1
fever | 1 | 2 | 3 | 2 | 2 | 4 | < 1
localized pain | 1 | 1 | 2 | 2 | 2 | 3 | < 1
Cardiovascular
dyspnea | 5 | 8 | 11 | 15 | 15 | 21 | 2
bradycardia | 8 | 8 | 9 | 7 | 5 | 16 | 2
chest pain | 4 | 3 | 10 | 10 | 14 | 16 | < 1
palpitation | 3 | 3 | 8 | 9 | 12 | 14 | < 1
edema | 2 | 2 | 5 | 3 | 5 | 8 | 1
ECG abnormal | 4 | 2 | 4 | 2 | 2 | 7 | 1
hypotension | 3 | 4 | 3 | 2 | 3 | 6 | 2
proarrhythmia | < 1 | < 1 | 2 | 4 | 5 | 5 | 3
syncope | 1 | 1 | 3 | 2 | 5 | 5 | 1
heart failure | 2 | 3 | 2 | 2 | 2 | 5 | 1
presyncope | 1 | 2 | 2 | 4 | 3 | 4 | < 1
peripheral vascular disorder | 1 | 2 | 1 | 1 | 2 | 3 | < 1
cardiovascular disorder | 1 | < 1 | 2 | 2 | 2 | 3 | < 1
vasodilation | 1 | < 1 | 1 | 2 | 1 | 3 | < 1
AICD discharge | < 1 | 2 | 2 | 2 | 2 | 3 | < 1
hypertension | < 1 | 1 | 1 | 1 | 2 | 2 | < 1
Nervous
fatigue | 5 | 8 | 12 | 12 | 13 | 20 | 2
dizziness | 7 | 6 | 11 | 11 | 14 | 20 | 1
asthenia | 4 | 5 | 7 | 8 | 10 | 13 | 1
light-headed | 4 | 3 | 6 | 6 | 9 | 12 | 1
headache | 3 | 2 | 4 | 4 | 4 | 8 | < 1
sleep problem | 1 | 1 | 5 | 5 | 6 | 8 | < 1
perspiration | 1 | 2 | 3 | 4 | 5 | 6 | < 1
altered consciousness | 2 | 3 | 1 | 2 | 3 | 4 | < 1
depression | 1 | 2 | 2 | 2 | 3 | 4 | < 1
paresthesia | 1 | 1 | 2 | 3 | 2 | 4 | < 1
anxiety | 2 | 2 | 2 | 3 | 2 | 4 | < 1
mood change | < 1 | < 1 | 1 | 3 | 2 | 3 | < 1
appetite disorder | 1 | 2 | 2 | 1 | 3 | 3 | < 1
stroke | < 1 | < 1 | 1 | 1 | < 1 | 1 | < 1
Digestive
nausea/vomiting | 5 | 4 | 4 | 6 | 6 | 10 | 1
diarrhea | 2 | 3 | 3 | 3 | 5 | 7 | < 1
dyspepsia | 2 | 3 | 3 | 3 | 3 | 6 | < 1
abdominal pain | < 1 | < 1 | 2 | 2 | 2 | 3 | < 1
colon problem | 2 | 1 | 1 | < 1 | 2 | 3 | < 1
flatulence | 1 | < 1 | 1 | 1 | 2 | 2 | < 1
Respiratory
pulmonary problem | 3 | 3 | 5 | 3 | 4 | 8 | < 1
upper respiratory tract problem | 1 | 1 | 3 | 4 | 3 | 5 | < 1
asthma | 1 | < 1 | 1 | 1 | 1 | 2 | < 1
Urogenital
genitourinary disorder | 1 | 0 | 1 | 1 | 2 | 3 | < 1
sexual dysfunction | < 1 | 1 | 1 | 1 | 3 | 2 | < 1
Metabolic
abnormal lab value | 1 | 2 | 3 | 2 | 1 | 4 | < 1
weight change | 1 | 1 | 1 | < 1 | 2 | 2 | < 1
Musculoskeletal
extremity pain | 2 | 2 | 4 | 5 | 3 | 7 | < 1
back pain | 1 | < 1 | 2 | 2 | 2 | 3 | < 1
Skin and Appendages
rash | 2 | 3 | 2 | 3 | 4 | 5 | < 1
Hematologic
bleeding | 1 | < 1 | 1 | < 1 | 2 | 2 | < 1
Special Senses
visual problem | 1 | 1 | 2 | 4 | 5 | 5 | < 1

a) Because patients are counted at each dose level tested, the Any Dose column cannot be determined by adding across the doses.

In an unblinded multicenter trial of 25 patients with SVT and/or VT receiving daily doses of 30, 90 and 210 mg/m^2 with dosing every 8 hours for a total of 9 doses, no Torsade de Pointes or other serious new arrhythmias were observed. One (1) patient, receiving 30 mg/m^2 daily, was discontinued because of increased frequency of sinus pauses/bradycardia. Additional cardiovascular AEs were seen at the 90 and 210 mg/m^2 daily dose levels. They included QT prolongations (2 patients), sinus pauses/bradycardia (1 patient), increased severity of atrial flutter and reported chest pain (1 patient). Values for QTC ≥ 525 msec were seen in 2 patients at the 210 mg/m^2 daily dose level. Serious adverse events including death, Torsade de Pointes, other proarrhythmias, high-degree A-V blocks and bradycardia have been reported in infants and/or children.

Potential Adverse Effects

Foreign marketing experience with sotalol hydrochloride shows an adverse experience profile similar to that described above from clinical trials. Voluntary reports since introduction include rare reports (less than one report per 10,000 patients) of: emotional lability, slightly clouded sensorium, incoordination, vertigo, paralysis, thrombocytopenia, eosinophilia, leukopenia, photosensitivity reaction, fever, pulmonary edema, hyperlipidemia, myalgia, pruritis, alopecia.

The oculomucocutaneous syndrome associated with the beta-blocker practolol has not been associated with sotalol during investigational use and foreign marketing experience.

OVERDOSAGE

Intentional or accidental overdosage with sotalol hydrochloride has rarely resulted in death.

Symptoms and Treatment of Overdosage

The most common signs to be expected are bradycardia, congestive heart failure, hypotension, bronchospasm and hypoglycemia. In cases of massive intentional overdosage (2 to 16 grams) of sotalol hydrochloride the following clinical findings were seen: hypotension, bradycardia, cardiac asystole, prolongation of QT interval, Torsade de Pointes, ventricular tachycardia, and premature ventricular complexes. If overdosage occurs, therapy with sotalol should be discontinued and the patient observed closely. Because of the lack of protein binding, hemodialysis is useful for reducing sotalol plasma concentrations. Patients should be carefully observed until QT intervals are normalized and the heart rate returns to levels >50 bpm. The occurrence of hypotension following an overdose may be associated with an initial slow drug elimination phase (half life of 30 hours) thought to be due to a temporary reduction of renal function caused by the hypotension. In addition, if required, the following therapeutic measures are suggested:

Bradycardia or Cardiac Asystole
Atropine, another anticholinergic drug, a beta-adrenergic agonist or transvenous cardiac pacing.

Heart Block
(second and third degree) transvenous cardiac pacemaker.

Hypotension
(depending on associated factors) epinephrine rather than isoproterenol or norepinephrine may be useful.

Bronchospasm
Aminophylline or aerosol beta-2-receptor stimulant.

Torsade de Pointes
DC cardioversion, transvenous cardiac pacing, epinephrine, magnesium sulfate.

DOSAGE AND ADMINISTRATION

As with other antiarrhythmic agents, sotalol hydrochloride tablets, USP should be initiated and doses increased in a hospital with facilities for cardiac rhythm monitoring and assessment (see INDICATIONS AND USAGE). Sotalol hydrochloride tablets, USP should be administered only after appropriate clinical assessment (see INDICATIONS AND USAGE), and the dosage of sotalol hydrochloride tablets, USP must be individualized for each patient on the basis of therapeutic response and tolerance. Proarrhythmic events can occur not only at initiation of therapy, but also with each upward dosage adjustment.

Adults

Dosage of sotalol hydrochloride tablets, USP should be adjusted gradually, allowing 3 days between dosing increments in order to attain steady-state plasma concentrations, and to allow monitoring of QT intervals. Graded dose adjustment will help prevent the usage of doses which are higher than necessary to control the arrhythmia. The recommended initial dose is 80 mg twice daily. This dose may be increased, if necessary, after appropriate evaluation to 240 or 320 mg/day (120 to 160 mg twice daily). In most patients, a therapeutic response is obtained at a total daily dose of 160 to 320 mg/day, given in two or three divided doses. Some patients with life-threatening refractory ventricular arrhythmias may require doses as high as 480 to 640 mg/day; however, these doses should only be prescribed when the potential benefit outweighs the increased risk of adverse events, in particular proarrhythmia. Because of the long terminal elimination half-life of sotalol, dosing on more than a BID regimen is usually not necessary.

Children

As in adults the following precautionary measures should be considered when initiating sotalol treatment in children: initiation of treatment in the hospital after appropriate clinical assessment; individualized regimen as appropriate; gradual increase of doses if required; careful assessment of therapeutic response and tolerability; and frequent monitoring of the QTc interval and heart rate.

For children aged about 2 years and greater
For children aged about 2 years and greater, with normal renal function, doses normalized for body surface area are appropriate for both initial and incremental dosing. Since the Class III potency in children (see CLINICAL PHARMACOLOGY) is not very different from that in adults, reaching plasma concentrations that occur within the adult dose range is an appropriate guide. From pediatric pharmacokinetic data the following is recommended.

For initiation of treatment, 30 mg/m^2 three times a day (90 mg/m^2 total daily dose) is approximately equivalent to the initial 160 mg total daily dose for adults. Subsequent titration to a maximum of 60 mg/m^2 (approximately equivalent to the 360 mg total daily dose for adults) can then occur. Titration should be guided by clinical response, heart rate and QTc, with increased dosing being preferably carried out in-hospital. At least 36 hours should be allowed between dose increments to attain steadystate plasma concentrations of sotalol in patients with age-adjusted normal renal function.

For children aged about 2 years or younger
For children aged about 2 years or younger, the above pediatric dosage should be reduced by a factor that depends heavily upon age, as shown in the following graph, age plotted on a logarithmic scale in months.

For a child aged 20 months, the dosing suggested for children with normal renal function aged 2 years or greater should be multiplied by about 0.97; the initial starting dose would be (30 X 0.97)=29.1 mg/m^2, administered three times daily. For a child aged 1 month, the starting dose should be multiplied by 0.68; the initial starting dose would be (30 X 0.68)=20 mg/m^2, administered three times daily. For a child aged about 1 week, the initial starting dose should be multiplied by 0.3; the starting dose would be (30 X 0.3)=9 mg/m^2. Similar calculations should be made for increased doses as titration proceeds. Since the half-life of sotalol decreases with decreasing age (below about 2 years), time to steady-state will also increase. Thus, in neonates the time to steady-state may be as long as a week or longer.

In all children, individualization of dosage is required. As in adults Betapace (sotalol hydrochloride) should be used with particular caution in children if the QTc is greater than 500 msec on therapy, and serious consideration should be given to reducing the dose or discontinuing therapy when QTc exceeds 550 msec.

Dosage in Renal Impairment

Adults

Because sotalol is excreted predominantly in urine and its terminal elimination half-life is prolonged in conditions of renal impairment, the dosing interval (time between divided doses) of sotalol should be modified (when creatinine clearance is lower than 60 mL/min) according to the following table.

Creatinine; Clearance; mL/min | Dosinga; Interval; (hours)
>60 | 12
30-59 | 24
10-29 | 36-48
<10 | Dose should be individualized

a) The initial dose of 80 mg and subsequent doses should be administered at these intervals. See following paragraph for dosage escalations.

Since the terminal elimination half-life of sotalol hydrochloride is increased in patients with renal impairment, a longer duration of dosing is required to reach steady-state. Dose escalations in renal impairment should be done after administration of at least 5 to 6 doses at appropriate intervals (see table above). Extreme caution should be exercised in the use of sotalol in patients with renal failure undergoing hemodialysis. The half-life of sotalol is prolonged (up to 69 hours) in anuric patients. Sotalol, however, can be partly removed by dialysis with subsequent partial rebound in concentrations when dialysis is completed. Both safety (heart rate, QT interval) and efficacy (arrhythmia control) must be closely monitored.

Children

The use of sotalol hydrochloride in children with renal impairment has not been investigated. Sotalol elimination is predominantly via the kidney in the unchanged form. Use of sotalol in any age group with decreased renal function should be at lower doses or at increased intervals between doses. Monitoring of heart rate and QTc is more important and it will take much longer to reach steady-state with any dose and/or frequency of administration.

Transfer to Sotalol Hydrochloride Tablets, USP

Before starting sotalol hydrochloride tablets, USP, previous antiarrhythmic therapy should generally be withdrawn under careful monitoring for a minimum of 2 to 3 plasma half-lives if the patient's clinical condition permits (see Drug Interactions). Treatment has been initiated in some patients receiving I.V. lidocaine without ill effect. After discontinuation of amiodarone, sotalol hydrochloride tablets, USP should not be initiated until the QT interval is normalized (see WARNINGS).

Preparation of Extemporaneous Oral Solution

Information relating to the preparation of an extemporaneous oral solution of sotalol is approved for Berlex Laboratories’ sotalol hydrochloride tablets. However, due to Berlex’s marketing exclusivity rights, this drug product is not labeled with that information.

Transfer to Betapace AF from Sotalol Hydrochloride Tablets, USP

Patients with a history of symptomatic AFIB/AFL who are currently receiving sotalol hydrochloride tablets, USP for the maintenance of normal sinus rhythm should be transferred to Betapace AF because of the significant differences in labeling (i.e., patient package insert for Betapace AF, dosing administration, and safety information).

HOW SUPPLIED

Sotalol Hydrochloride Tablets, USP 80 mg are available for oral administration as white to off-white capsule shaped, scored tablets, imprinted “APO” on one side and “SO” bisect “80” on the other side; supplied in bottles of 30 (NDC 63187-804-30), bottles of 60 (NDC 63187-804-60) and bottles of 90 (63187-804-90).

Store at 20° to 25°C (68° to 77°F); excursions permitted from 15° to 30°C (59° to 86°F) [see USP Controlled Room Temperature].

Dispense in tight, light-resistant container [see USP].

Betapace AF® is a trademark of Berlex.

APOTEX INC.
SOTALOL HYDROCHLORIDE TABLETS, USP
80 mg

Manufactured by | Manufactured for | Repackaged by
Apotex Inc. | Apotex Corp. | Proficient Rx LP
Toronto, Ontario | Weston, Florida | Thousand Oaks, CA 91320
Canada M9L 1T9 | 33326

Revised: April 2015

Rev. 3

PRINCIPAL DISPLAY PANEL - 80 mg Bottle Label

Representative sample of labeling (see HOW SUPPLIED section for complete listing):

NDC 63187-804-30

Sotalol Hydrochloride Tablets, USP

80 mg

Rx

30 count bottle